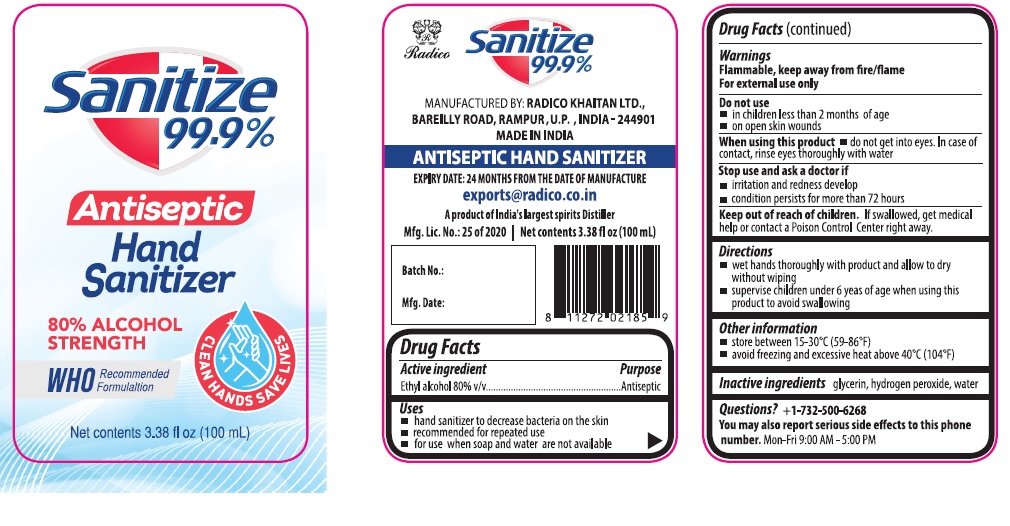 DRUG LABEL: Sanitize 99.9% Antiseptic Hand Sanitizer
NDC: 79390-999 | Form: LIQUID
Manufacturer: Radico Khaitan Limited
Category: otc | Type: HUMAN OTC DRUG LABEL
Date: 20200707

ACTIVE INGREDIENTS: ALCOHOL 80 mL/100 mL
INACTIVE INGREDIENTS: GLYCERIN; HYDROGEN PEROXIDE; WATER

Sanitize 99.9% Antiseptic Hand Sanitizer

Active ingredient

Ethyl alcohol 80% v/v

Purpose

Antiseptic

Uses

- hand sanitizer to decrease bacteria on the skin
- recommended for repeated use
- for use when soap and water are not available

Warnings

Flammable, keep away from fire/flame

For external use only

Do not use

- in children less than 2 months of age
- on open skin wounds

When using this product • do not get into eyes. In case of contact, rinse eyes thoroughly with water

Stop use and ask a doctor if

- irritation and redness develop
- condition persists for more than 72 hours

Keep out of reach of children. If swallowed, get medical help or contact a Poison Control Center right away.

Directions

- wet hands thoroughly with product and allow to dry without wiping
- supervise children under 6 yeas of age when using this product to avoid swallowing

Other information

- store between 15-30°C (59-86°F)
- avoid freezing and excessive heat above 40°C (104°F)

Inactive ingredients

glycerin, hydrogen peroxide, water

Questions?

+1-732-500-6268
You may also report serious side effects to this phone number. Mon-Fri 9:00 AM - 5:00 PM

80% ALCOHOL STRENGTH

WHO recommended Formulation

CLEAN HANDS SAVE LIVES

MANUFACTURED BY: RADICO KHAITAN LTD., BAREILY ROAD, RAMPUR, U.P, INDIA-244901

MADE IN INDIA

EXPIRY DATE: 24 MONTHS FROM THE DATE OF MANUFACTURE

exports@radico.co.in

A product of India's largest spirits Distiller